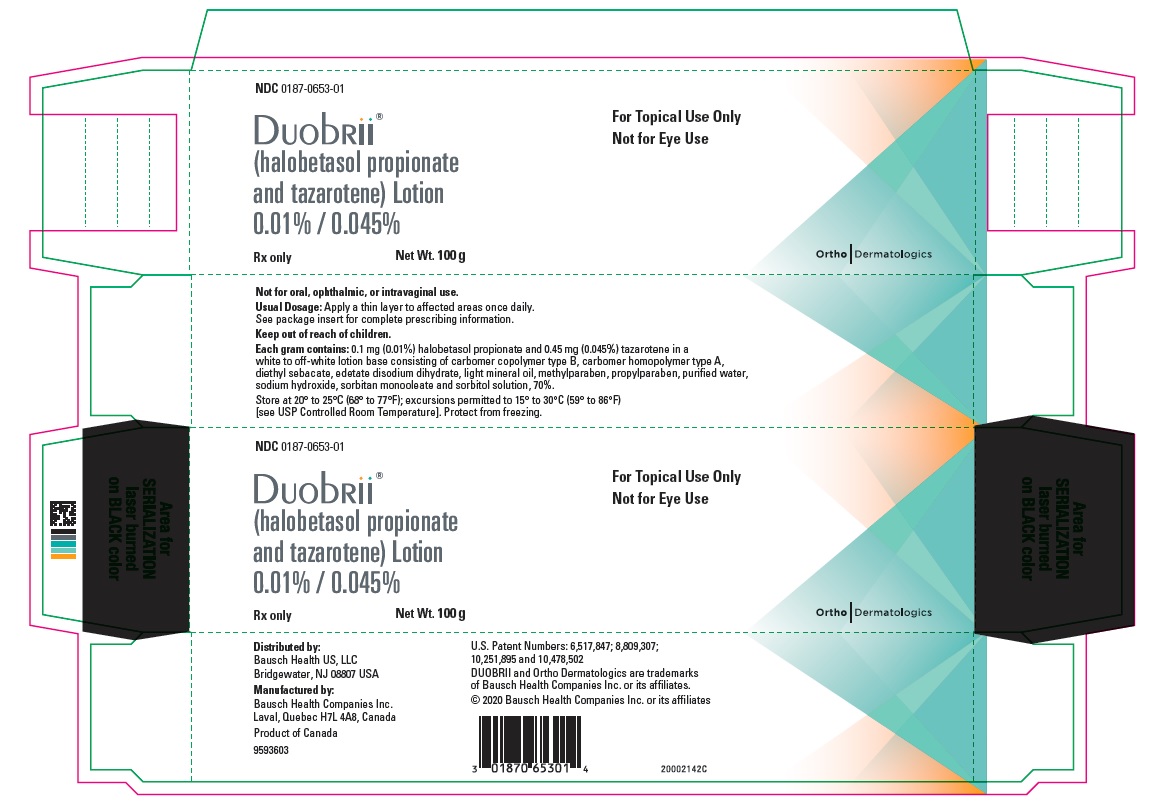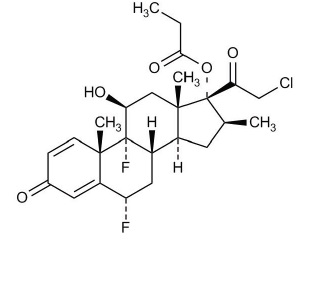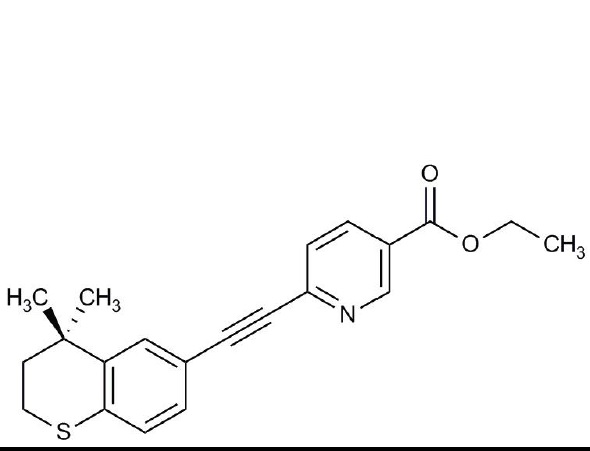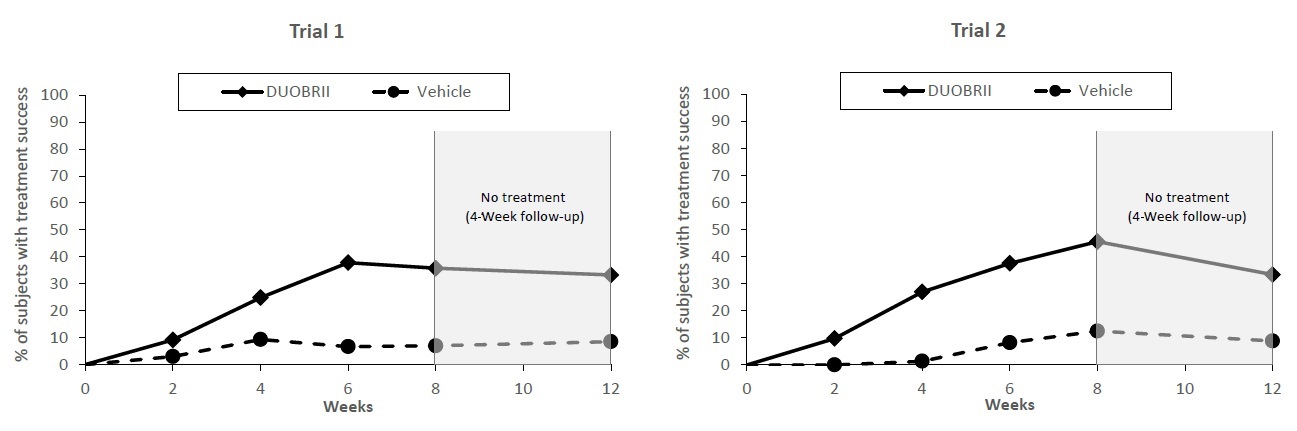 DRUG LABEL: Duobrii
NDC: 0187-0653 | Form: LOTION
Manufacturer: Bausch Health US, LLC
Category: prescription | Type: HUMAN PRESCRIPTION DRUG LABEL
Date: 20200101

ACTIVE INGREDIENTS: HALOBETASOL PROPIONATE 0.1 mg/1 g; TAZAROTENE 0.45 mg/1 g
INACTIVE INGREDIENTS: CARBOMER COPOLYMER TYPE B (ALLYL PENTAERYTHRITOL CROSSLINKED); CARBOMER HOMOPOLYMER TYPE A (ALLYL PENTAERYTHRITOL CROSSLINKED); DIETHYL SEBACATE; EDETATE DISODIUM; LIGHT MINERAL OIL; METHYLPARABEN; PROPYLPARABEN; WATER; SODIUM HYDROXIDE; SORBITAN MONOOLEATE; SORBITOL

HIGHLIGHTS OF PRESCRIBING INFORMATION

These highlights do not include all the information needed to use DUOBRII safely and effectively. See full prescribing information for DUOBRII.
DUOBRII® (halobetasol propionate and tazarotene) lotion, for topical use
Initial U.S. Approval: 2019

1 INDICATIONS AND USAGE

DUOBRII Lotion is a combination of halobetasol propionate and tazarotene indicated for the topical treatment of plaque psoriasis in adults. (1)

2 DOSAGE AND ADMINISTRATION

- Apply a thin layer of DUOBRII Lotion to the affected areas once daily. (2)
- Not for oral, ophthalmic, or intravaginal use. (2)

3 DOSAGE FORMS AND STRENGTHS

Lotion, 0.01%/0.045% (3)

Each gram of DUOBRII Lotion contains 0.1 mg (0.01%) halobetasol propionate and 0.45 mg (0.045%) tazarotene. (3)

4 CONTRAINDICATIONS

DUOBRII Lotion is contraindicated in pregnancy (4.1, 8.1)

5 WARNINGS AND PRECAUTIONS

- Embryofetal risk: DUOBRII Lotion contains tazarotene, which is a teratogenic substance. In females of reproductive potential, obtain a negative pregnancy test within 2 weeks prior to initiating treatment and advise patients to use an effective method of contraception during treatment. (5.1)
- Reversible hypothalamic-pituitary-adrenal (HPA) axis suppression may occur, with the potential for glucocorticosteroid insufficiency during or after treatment. (5.2)
- Systemic effects of topical corticosteroids may also include Cushing’s syndrome, hyperglycemia, and glucosuria. (5.2)
- Systemic absorption may require evaluation for HPA axis suppression. (5.2)
- Use of potent corticosteroids on large areas, for prolonged durations, under occlusive dressings, or on an altered skin barrier may increase systemic exposure. (5.2)
- Local Adverse Reactions: Local adverse reactions may include atrophy, striae, telangiectasias, and folliculitis. If these effects occur, discontinue at least until the integrity of the skin has been restored. DUOBRII Lotion should not be used on eczematous skin, as it may cause severe irritation. (5.3)
- Photosensitivity and Risk for Sunburn: Avoid exposure to sunlight, sunlamps, and weather extremes. DUOBRII Lotion should be administered with caution if the patient is also taking drugs known to be photosensitizers. (5.4)
- Ophthalmic Adverse Reactions: Use of topical corticosteroids may increase the risk of posterior subcapsular cataracts and glaucoma. If visual symptoms occur, consider referral to an ophthalmologist (5.5).

6 ADVERSE REACTIONS

- The most common adverse reactions are contact dermatitis (7%), application site pain (3%), folliculitis (2%), skin atrophy (2%), and excoriation (2%). (6.1)

To report SUSPECTED ADVERSE REACTIONS, contact Bausch Health US, LLC at 1-800-321-4576 or FDA at 1-800-FDA-1088 or www.fda.gov/medwatch.

FULL PRESCRIBING INFORMATION

1 INDICATIONS AND USAGE

DUOBRII® (halobetasol propionate and tazarotene) Lotion, 0.01%/0.045% is indicated for the topical treatment of plaque psoriasis in adults.

2 DOSAGE AND ADMINISTRATION

Apply a thin layer of DUOBRII Lotion once daily to cover only affected areas and rub in gently. If a bath or shower is taken prior to application, the skin should be dry before applying the lotion.

The total dosage should not exceed approximately 50 g per week because of the potential for the drug to suppress the hypothalamic-pituitary-adrenal (HPA) axis [see Warnings and Precautions (5.2)]. Do not use with occlusive dressings unless directed by a physician. Discontinue treatment when control is achieved. Avoid application of DUOBRII Lotion on the face, groin, or in the axillae.

DUOBRII Lotion is not for oral, ophthalmic, or intravaginal use.

3 DOSAGE FORMS AND STRENGTHS

Lotion, 0.01%/0.045%

Each gram of DUOBRII Lotion contains 0.1 mg (0.01%) halobetasol propionate and 0.45 mg (0.045%) tazarotene in a white to off-white lotion.

4 CONTRAINDICATIONS

4.1 Pregnancy

DUOBRII Lotion is contraindicated in pregnancy [see Warnings and Precautions (5.1), Use in Specific Populations (8.1, 8.3)].

5 WARNINGS AND PRECAUTIONS

5.1 Embryofetal Risk

Based on data from animal reproduction studies, retinoid pharmacology, and the potential for systemic absorption, DUOBRII Lotion may cause fetal harm when administered to a pregnant female and is contraindicated during pregnancy. Tazarotene is teratogenic, and it is not known what level of exposure is required for teratogenicity in humans [see Contraindications (4), Clinical Pharmacology (12.3)]. Tazarotene elicits teratogenic and developmental effects associated with retinoids after topical or systemic administration in rats and rabbits [see Use in Specific Populations (8.1)].

Advise pregnant females of the potential risk to a fetus. Obtain a pregnancy test within 2 weeks prior to DUOBRII Lotion therapy. Initiate DUOBRII Lotion therapy during a menstrual period. Advise females of reproductive potential to use effective contraception during treatment with DUOBRII Lotion therapy [see Use in Specific Populations (8.1 and 8.3)].

5.2 Hypothalamic-Pituitary-Adrenal (HPA) Axis Suppression and Other Unwanted Systemic Glucocorticoid Effects

DUOBRII Lotion contains halobetasol propionate, a corticosteroid, and has been shown to suppress the hypothalamic-pituitary-adrenal (HPA) axis.

Systemic effects of topical corticosteroids may include reversible HPA axis suppression with the potential for glucocorticosteroid insufficiency. This may occur during treatment or upon withdrawal of treatment of the topical corticosteroid.

The potential for hypothalamic-pituitary-adrenal (HPA) axis suppression with DUOBRII Lotion was evaluated in a study of 20 adult subjects with moderate to severe plaque psoriasis involving ≥20% of their body surface area. The subjects were treated once daily for 8 weeks and assessed for HPA axis suppression at Weeks 4 and 8. HPA axis suppression occurred in 3 out of 20 (15%) subjects at Week 4 and none (0%) of these 20 subjects had HPA axis suppression at Week 8 [see Clinical Pharmacology (12.2)].

Because of the potential for systemic absorption, use of topical corticosteroids, including DUOBRII Lotion, may require that patients be evaluated periodically for evidence of HPA axis suppression. Factors that predispose a patient using a topical corticosteroid to HPA axis suppression include the use of more potent corticosteroids, use over large surface areas, occlusive use, use on an altered skin barrier, concomitant use of multiple corticosteroid-containing products, liver failure, and young age. An adrenocorticotropic hormone (ACTH) stimulation test may be helpful in evaluating patients for HPA axis suppression.

If HPA axis suppression is documented, attempt to gradually withdraw the drug or reduce the frequency of application. Manifestations of adrenal insufficiency may require supplemental systemic corticosteroids. Recovery of HPA axis function is generally prompt and complete upon discontinuation of topical corticosteroids.

Systemic effects of topical corticosteroids may also include Cushing’s syndrome, hyperglycemia, and glucosuria. Use of more than one corticosteroid-containing product at the same time may increase the total systemic exposure to topical corticosteroids. Pediatric patients may be more susceptible than adults to systemic toxicity from the use of topical corticosteroids because of their larger surface-to-body-mass ratio [see Use in Specific Populations (8.4)].

5.3 Local Adverse Reactions

Local adverse reactions may include atrophy, striae, telangiectasias, folliculitis and contact dermatitis. Some local adverse reactions may be irreversible. If these adverse reactions occur, discontinue the medication at least until the integrity of the skin is restored; do not resume treatment if allergic contact dermatitis is identified.

Avoid use of DUOBRII Lotion on eczematous skin, as it may cause severe irritation.

5.4 Photosensitivity and Risk for Sunburn

Because of heightened burning susceptibility, exposure to sunlight (including sunlamps) should be avoided unless deemed medically necessary, and in such cases, exposure should be minimized during the use of DUOBRII Lotion. Patients must be instructed to use sunscreens and protective clothing when using DUOBRII Lotion. Patients with sunburn should be advised not to use DUOBRII Lotion until fully recovered. Patients who may have considerable sun exposure due to their occupation and those patients with inherent sensitivity to sunlight should exercise particular caution when using DUOBRII Lotion.

DUOBRII Lotion should be administered with caution if the patient is also taking drugs known to be photosensitizers (e.g., thiazides, tetracyclines, fluoroquinolones, phenothiazines, sulfonamides) because of the increased possibility of augmented photosensitivity.

5.5 Ophthalmic Adverse Reactions

Use of topical corticosteroids may increase the risk of posterior subcapsular cataracts and glaucoma. Cataracts and glaucoma have been reported postmarketing with the use of topical corticosteroid products. Advise patients to report any visual symptoms and consider referral to an ophthalmologist for evaluation.

5.6 Concomitant Skin Infections

Use an appropriate antimicrobial agent if a skin infection is present or develops. If a favorable response does not occur promptly, discontinue use of DUOBRII Lotion until the infection has been adequately treated.

6 ADVERSE REACTIONS

6.1 Clinical Trials Experience

Because clinical trials are conducted under widely varying conditions, adverse reaction rates observed in the clinical trials of a drug cannot be directly compared to rates in the clinical trials of another drug and may not reflect the rates observed in clinical practice.

In randomized, double-blind, multicenter, vehicle-controlled clinical trials, 410 adults with plaque psoriasis were treated with DUOBRII Lotion or vehicle lotion and had post-baseline safety data. Subjects applied DUOBRII Lotion or vehicle lotion once daily for up to 8 weeks. Table 1 presents adverse reactions that occurred in at least 1% of subjects treated with DUOBRII Lotion and more frequently than in vehicle-treated subjects.

Table 1: Adverse Reactions Occurring in ≥1% of the Subjects Treated with DUOBRII Lotion through Week 8
Adverse Reaction | DUOBRII Lotion; (N=270) | Vehicle Lotion; (N=140)
Contact Dermatitis | 20 (7%) | 0
Application Site Pain | 7 (3%) | 1 (1%)
Folliculitis | 5 (2%) | 0
Skin Atrophy | 5 (2%) | 0
Excoriation | 5 (2%) | 0
Rash | 4 (1%) | 0
Skin Abrasion | 3 (1%) | 0
Skin Exfoliation | 2 (1%) | 0

8 USE IN SPECIFIC POPULATIONS

8.1 Pregnancy

Risk Summary

Based on data from animal reproduction studies, retinoid pharmacology, and the potential for systemic absorption, DUOBRII Lotion may cause fetal harm when administered to a pregnant female and is contraindicated during pregnancy. Safety in pregnant females has not been established. The potential risk to the fetus outweighs the potential benefit to the mother from DUOBRII Lotion during pregnancy; therefore, DUOBRII Lotion should be discontinued as soon as pregnancy is recognized [see Contraindications (4), Warnings and Precautions (5.1), Clinical Pharmacology (12.3)].

Observational studies suggest an increased risk of low birthweight in infants with the maternal use of potent or very potent topical corticosteroids (see Data).

In animal reproduction studies with pregnant rats, reduced fetal body weights and reduced skeletal ossification were observed after topical administration of a tazarotene gel formulation during the period of organogenesis at a dose 11 times the maximum recommended human dose (MRHD) (based on AUC comparison). In animal reproduction studies with pregnant rabbits, single incidences of known retinoid malformations, including spina bifida, hydrocephaly, and heart anomalies were observed after topical administration of a tazarotene gel formulation at 116 times the MRHD (based on AUC comparison) (see Data).

In animal reproduction studies with pregnant rats and rabbits, malformations, fetal toxicity, developmental delays, and/or behavioral delays were observed after oral administration of tazarotene during the period of organogenesis at doses 9 and 228 times, respectively, the MRHD (based on AUC comparison). In pregnant rats, decreased litter size, decreased numbers of live fetuses, decreased fetal body weights, and increased malformations were observed after oral administration of tazarotene prior to mating through early gestation at doses 9 times the MRHD (based on AUC comparison) (see Data).

In animal reproduction studies, increased malformations, including cleft palate and omphalocele, were observed after oral administration of halobetasol propionate during the period of organogenesis to pregnant rats and rabbits (see Data). The available data do not support relevant comparisons of systemic halobetasol propionate exposures achieved in the animal studies to exposures observed in humans after topical use of DUOBRII Lotion.

The background risk of major birth defects and miscarriage for the indicated population is unknown. All pregnancies have a background risk of birth defect, loss, or other adverse outcomes. The background risk in the U.S. general population of major birth defects is 2 to 4%, and of miscarriage is 15 to 20%, of clinically recognized pregnancies.

Data

Human Data

Available observational studies in pregnant women did not identify a drug-associated risk of major birth defects, preterm delivery, or fetal mortality with the use of topical corticosteroids of any potency. However, when the dispensed amount of potent or very potent topical corticosteroids exceeded 300 g during the entire pregnancy, maternal use was associated with an increased risk of low birth weight in infants.

Animal Data

Halobetasol propionate has been shown to cause malformations in rats and rabbits when given orally during organogenesis at doses of 0.04 to 0.1 mg/kg/day in rats and 0.01 mg/kg/day in rabbits. Halobetasol propionate was embryotoxic in rabbits but not in rats. Cleft palate was observed in both rats and rabbits. Omphalocele was seen in rats but not in rabbits.

In an embryofetal development study in rats, a tazarotene gel formulation, 0.5% (0.25 mg/kg/day tazarotene) was topically administered to pregnant rats during gestation days 6 through 17. Reduced fetal body weights and reduced skeletal ossification occurred at this dose (11 times the MRHD based on AUC comparison). In an embryofetal development study in rabbits, a tazarotene gel formulation (0.5%, 0.25 mg/kg/day tazarotene) was topically administered to pregnant rabbits during gestation days 6 through 18. Single incidences of known retinoid malformations, including spina bifida, hydrocephaly, and heart anomalies were noted at this dose (116 times the MRHD based on AUC comparison).

When tazarotene was given orally to animals, developmental delays were seen in rats; malformations and post-implantation loss were observed in rats and rabbits at doses producing 9 and 228 times, respectively, the MRHD (based on AUC comparisons).

In female rats orally administered 2 mg/kg/day of tazarotene from 15 days before mating through gestation day 7, classic developmental effects of retinoids including decreased number of implantation sites, decreased litter size, decreased numbers of live fetuses, and decreased fetal body weights were observed at this dose (16 times the MRHD based on AUC comparison). A low incidence of retinoid-related malformations was observed at that dose.

In a pre- and postnatal development toxicity study, topical administration of a tazarotene gel formulation (0.125 mg/kg/day) to pregnant female rats from gestation day 16 through lactation day 20 reduced pup survival but did not affect the reproductive capacity of the offspring. Based on data from another study, the systemic drug exposure in the rat at this dose would be equivalent to 5 times the MRHD (based on AUC comparison).

8.2 Lactation

Risk Summary

There are no data on the presence of tazarotene, halobetasol propionate or its metabolites in human milk, the effects on the breastfed infant, or the effects on milk production after treatment with DUOBRII Lotion.

After single topical doses of a ^14C-tazarotene gel formulation to the skin of lactating rats, radioactivity was detected in rat milk.

It is not known whether topical administration of corticosteroids could result in sufficient systemic absorption to produce detectable quantities in human milk.

The developmental and health benefits of breastfeeding should be considered along with the mother’s clinical need for DUOBRII Lotion and any potential adverse effects on the breastfed child from DUOBRII Lotion.

Clinical Considerations

Advise breastfeeding women not to apply DUOBRII Lotion directly to the nipple and areola to avoid direct infant exposure.

8.3 Females and Males of Reproductive Potential

Pregnancy Testing

DUOBRII Lotion is contraindicated in women who are pregnant. Females of reproductive potential should be warned of the potential risk and use adequate birth control measures during treatment with DUOBRII Lotion. The possibility that a female of reproductive potential is pregnant at the time of institution of therapy should be considered. A negative result for pregnancy should be obtained within 2 weeks prior to DUOBRII Lotion therapy, which should begin during menstruation.

Contraception

Based on animal studies, DUOBRII Lotion may cause fetal harm when administered to a pregnant female [see Use in Specific Populations (8.1)]. Advise females of reproductive potential to use effective contraception during treatment with DUOBRII Lotion.

8.4 Pediatric Use

Safety and effectiveness of DUOBRII Lotion in pediatric patients under the age of 18 years have not been evaluated.

Because of higher skin-surface-area-to-body-mass ratios, pediatric patients are at a greater risk than adults of HPA axis suppression and Cushing’s syndrome when they are treated with topical corticosteroids. They are therefore also at greater risk of adrenal insufficiency during or after withdrawal of treatment. Adverse reactions including striae have been reported with use of topical corticosteroids in infants and children [see Warnings and Precautions (5.2)].

HPA axis suppression, Cushing’s syndrome, linear growth retardation, delayed weight gain, and intracranial hypertension have been reported in children receiving topical corticosteroids. Manifestations of adrenal suppression in children include low plasma cortisol levels and an absence of response to ACTH stimulation. Manifestations of intracranial hypertension include bulging fontanelles, headaches, and bilateral papilledema [see Warnings and Precautions (5.2)].

8.5 Geriatric Use

Of the 270 subjects exposed to DUOBRII Lotion in clinical trials, 39 subjects were 65 years or older. Clinical trials of DUOBRII Lotion did not include sufficient numbers of subjects age 65 years and older to determine whether they respond differently from younger subjects.

11 DESCRIPTION

DUOBRII Lotion is a combination product with halobetasol propionate and tazarotene as the active ingredients in a white to off-white lotion formulation intended for topical use.

Halobetasol propionate is a synthetic corticosteroid. The chemical name for halobetasol propionate is [(6S,9R,16S,17R)-17-(2-chloroacetyl)-6,9-difluoro-11-hydroxy-10,13,16-trimethyl-3-oxo-6,7,8,11,12,14,15,16-octahydrocyclopenta[a]phenanthren-17-yl] propanoate. The structural formula for halobetasol propionate is represented below:

Molecular Formula: C25H31ClF2O5 Molecular Weight: 484.96

Tazarotene is a member of the acetylenic class of retinoids. The chemical name for tazarotene is 6-[(3,4-Dihydro-4,4-dimethyl-2H-1-benzothiopyran-6-yl)ethynyl]-3-pyridinecarboxylic acid ethyl ester. The structural formula for tazarotene is represented below:

Molecular Formula: C21H21NO2S Molecular Weight: 351.46

Each gram of DUOBRII Lotion contains 0.1 mg (0.01%) halobetasol propionate and 0.45 mg (0.045%) tazarotene in a white to off-white lotion base consisting of carbomer copolymer type B, carbomer homopolymer type A, diethyl sebacate, edetate disodium dihydrate, light mineral oil, methylparaben, propylparaben, purified water, sodium hydroxide, sorbitan monooleate and sorbitol solution, 70%.

12 CLINICAL PHARMACOLOGY

12.1 Mechanism of Action

Corticosteroids play a role in cellular signaling, immune function, inflammation, and protein regulation; however, the precise mechanism of action in plaque psoriasis is unknown.

Tazarotene is a retinoid prodrug which is converted to its active form, tazarotenic acid, the carboxylic acid of tazarotene, by deesterification. Tazarotenic acid binds to all three members of the retinoic acid receptor (RAR) family: RARα, RARβ and RARγ, but shows relative selectivity for RARβ, and RARγ and may modify gene expression. The clinical significance of these findings for the treatment of plaque psoriasis is unknown.

12.2 Pharmacodynamics

A vasoconstrictor assay in healthy subjects with DUOBRII Lotion indicated that it is in the high to super-high range of potency as compared to other topical corticosteroids; however, similar blanching scores do not necessarily imply therapeutic equivalence.

The potential for hypothalamic-pituitary-adrenal (HPA) axis suppression was evaluated in a study in adult subjects with moderate to severe plaque psoriasis. A median dose of 8.2 grams DUOBRII Lotion was applied once daily for 8 weeks and 20 subjects were assessed for HPA axis suppression at Weeks 4 and 8. HPA axis suppression was observed in 3 out of 20 (15%) subjects at Week 4. None of the 20 (0%) subjects had HPA axis suppression at Week 8. In this study, the criteria for HPA axis suppression was a serum cortisol level of less than or equal to 18 micrograms per deciliter 30 minutes after stimulation with cosyntropin (adrenocorticotropic hormone). [See Warnings and Precautions (5.2).]

The pharmacodynamics of tazarotene is unknown.

12.3 Pharmacokinetics

Following topical application, tazarotene undergoes esterase hydrolysis to form its active metabolite, tazarotenic acid.

Systemic exposure following topical application of DUOBRII Lotion was evaluated in the same study that evaluated the HPA axis suppression. It was an open-label, randomized, pharmacokinetics (PK) study conducted in subjects aged 18 years and older with moderate to severe plaque psoriasis affecting at least 20% body surface area. The PK of halobetasol propionate, tazarotene, and tazarotenic acid was evaluated in 22 subjects following application of DUOBRII Lotion to the affected area once daily for 28 days. Systemic concentrations of halobetasol propionate (lower limit of quantification (LLOQ) = 50 pg/mL) and tazarotene (LLOQ = 5 pg/mL) on Day 28 were quantifiable in 13 and 18 out of a total number of 22 subjects, respectively. Tazarotenic acid (LLOQ = 5 pg/mL) was quantifiable in all subjects. Systemic exposure of the three moieties was at or near steady state by Day 28. The mean (standard deviation) of PK parameters on Day 28 is shown in Table 2.

Table 2:PK Parameters of Halobetasol Propionate, Tazarotene, and Tazarotenic Acid Following Once Daily Administration of DUOBRII Lotion for 28 Days in Subjects with Moderate to Severe Plaque Psoriasis
 |  | Mean (Standard Deviation) (N=22)
 | PK Parameters | Halobetasol Propionate | Tazarotene | Tazarotenic Acid
Day 28 | Cmax (pg/mL) | 101.9 (135.4) | 24.6 (27.3) | 523.4 (523.3)
Day 28 | AUC0-24 (pg*hr/mL) | 1300 (1959) | 273 (403) | 9954 (10091)

13 NONCLINICAL TOXICOLOGY

13.1 Carcinogenesis, Mutagenesis, Impairment of Fertility

Long-term animal studies have not been performed to evaluate the carcinogenic potential of halobetasol propionate.

A long-term study of tazarotene following oral administration of 0.025, 0.050, and 0.125 mg/kg/day to rats showed no indications of increased carcinogenic risks. Based on pharmacokinetic data from a shorter term study in rats, the highest dose of 0.125 mg/kg/day was anticipated to give systemic exposure in the rat equivalent to 1.4 times the MRHD (based on AUC comparison).

A long-term study with topical application of up to 0.1% of tazarotene in a gel formulation in mice terminated at 88 weeks showed that dose levels of 0.05, 0.125, 0.25, and 1 mg/kg/day (reduced to 0.5 mg/kg/day for males after 41 weeks due to severe dermal irritation) revealed no apparent carcinogenic effects when compared to vehicle control animals. Tazarotenic acid systemic exposures at the highest dose was 35 times the MRHD (based on AUC comparison).

Halobetasol propionate was not genotoxic in the Ames assay, in the sister chromatid exchange test in Chinese hamster somatic cells, in chromosome aberration studies of germinal and somatic cells of rodents, and in a mammalian spot test. Positive mutagenicity effects were observed in a mouse lymphoma gene mutation assay in vitro and in a Chinese hamster micronucleus test.

Tazarotene was non-mutagenic in the Ames assay and did not produce structural chromosomal aberrations in human lymphocytes. Tazarotene was non-mutagenic in the CHO/HGPRT mammalian cell forward gene mutation assay and was non-clastogenic in an in vivo mouse micronucleus test.

Studies in rats following oral administration of halobetasol propionate at dose levels up to 0.05 mg/kg/day, approximately 0.53 times the MRHD based on BSA comparisons, indicated no impairment of fertility or general reproductive performance.

No impairment of fertility occurred in rats when male animals were treated for 70 days prior to mating and female animals were treated for 14 days prior to mating and continuing through gestation and lactation with topical doses of a tazarotene gel formulation up to 0.125 mg/kg/day. Based on data from another study, the systemic drug exposure in the rat at the highest dose was 5 times the MRHD (based on AUC comparison).

No impairment of mating performance or fertility was observed in male rats treated for 70 days prior to mating with oral doses of up to 1 mg/kg/day tazarotene, which produced a systemic exposure 17 times the MRHD (based on AUC comparison).

No impairment of mating performance or fertility was observed in female rats treated for 15 days prior to mating and continuing through gestation day 7 with oral doses of tazarotene up to 2 mg/kg/day. However, there was a significant decrease in the number of estrous stages and an increase in developmental effects at that dose, which produced a systemic exposure 30 times the MRHD (based on AUC comparison).

14 CLINICAL STUDIES

The safety and efficacy of once daily use of DUOBRII Lotion for the treatment of moderate to severe plaque psoriasis were assessed in two prospective, multicenter, randomized, double-blind clinical trials (Trial 1 [NCT02462070] and Trial 2 [NCT02462122]). These trials were conducted in 418 subjects 18 years of age and older with moderate to severe plaque psoriasis that covered a body surface area (BSA) between 3% and 12% excluding the face, scalp, palms, soles, axillae, and intertriginous areas. Disease severity was determined by a 5-grade Investigator’s Global Assessment (IGA). Subjects applied DUOBRII Lotion or vehicle to all affected areas once daily for up to 8 weeks. All subjects returned for a 4-week follow-up visit (Week 12 visit) where safety and efficacy were evaluated.

The primary efficacy endpoint was the proportion of subjects with “treatment success” at Week 8. Treatment success was defined as at least a 2-grade improvement from baseline in the IGA score and an IGA score equating to “clear” or “almost clear”. Table 3 lists the primary efficacy results for Trials 1 and 2. The secondary efficacy endpoints evaluated treatment success sequentially at Weeks 12, 6, 4, and 2. Figure 1 shows the primary and secondary efficacy results over time.

Table 3: Primary Efficacy Outcomes in Subjects with Moderate to Severe Plaque Psoriasis at Week 8
 | Trial 1 |  | Trial 2
 | DUOBRII | Vehicle | DUOBRII | Vehicle
 | N=135 | N=68 | N=141 | N=74
IGA Treatment Success at Week 8 [Treatment success was defined as at least a 2-grade improvement from baseline in IGA score and an IGA score equating to “clear” or “almost clear”. Clear = no evidence of scaling, no evidence of erythema, no evidence of plaque elevation above normal skin level. Almost clear = some plaques with fine scales, faint pink/light red erythema on most plaques, slight or barely perceptible elevation of plaques above normal skin level.] | 36% | 7% | 45% | 13%

Figure 1: Efficacy Results* over Time

*The treatment difference at Week 2 in Trial 1 was not statistically significant.

16 HOW SUPPLIED/STORAGE AND HANDLING

DUOBRII (halobetasol propionate and tazarotene) Lotion, 0.01%/0.045% is a white to off-white lotion supplied in a white aluminum tube as follows:

- 100 g (NDC 0187-0653-01)

Storage and Handling Conditions

Store at 20° to 25°C (68° to 77°F); excursions permitted to 15° to 30°C (59° to 86°F) [see USP Controlled Room Temperature]. Protect from freezing.

17 PATIENT COUNSELING INFORMATION

Advise the patient to read the FDA-approved patient labeling (Patient Information).

This information is intended to aid in the safe and effective use of this medication. It is not a disclosure of all administration instructions or all possible adverse or unintended effects.

Advise patients using DUOBRII Lotion of the following information and instructions:

Important Administration Instructions

If undue irritation (redness, peeling, or discomfort) occurs, reduce frequency of application or temporarily interrupt treatment. Treatment may be resumed once irritation subsides [see Dosage and Administration (2) and Warnings and Precautions (5.2)].

Inform patients that total dosage should not exceed 50 grams per week [see Dosage and Administration (2)].

Instruct patients to avoid bandaging, wrapping or otherwise occluding the treatment area(s), unless directed by physician. Advise patients to avoid use on the face, groin, or axillae [see Dosage and Administration (2)].

Inform patients that DUOBRII Lotion is for external use only. Advise patients that DUOBRII Lotion is not for oral, ophthalmic, or intravaginal use [see Dosage and Administration (2)].

Fetal risk is associated with DUOBRII Lotion for females of reproductive potential. Advise patients to use an effective method of contraception during treatment to avoid pregnancy. Advise the patient to stop medication if she becomes pregnant and call her doctor [see Contraindications (4.1), Warnings and Precautions (5.1) and Use in Specific Populations (8.1)].

Breastfeeding women should not apply DUOBRII Lotion directly to the nipple and areola to avoid directly exposing the infant [see Use in Specific Populations (8.2)].

Avoid exposure of the treated areas to either natural or artificial sunlight, including tanning beds and sunlamps. Use sunscreen and protective clothing if exposure to sunlight is unavoidable when using DUOBRII Lotion [see Warnings and Precautions (5.4)].

HPA Axis Suppression and Other Unwanted Systemic Glucocorticoid Effects

DUOBRII Lotion may cause HPA axis suppression. Advise patients that use of topical corticosteroids, including DUOBRII Lotion, may require periodic evaluation for HPA axis suppression. Topical corticosteroids may have other endocrine effects. Concomitant use of multiple corticosteroid-containing products may increase the total systemic exposure to topical corticosteroids [see Warnings and Precautions (5.2)].

Local Adverse Reactions

Inform patients that DUOBRII Lotion may cause local adverse reactions. These reactions may be more likely to occur with occlusive use or use of DUOBRII Lotion. If undue irritation (redness, peeling, or discomfort) occurs, reduce frequency of application or temporarily interrupt treatment. Treatment may be resumed once irritation subsides, unless allergic contact dermatitis is identified [see Warnings and Precautions (5.3)].

Ophthalmic Adverse Reactions

Advise patients to report any visual symptoms to their healthcare providers.

Distributed by:
Bausch Health US, LLC
Bridgewater, NJ 08807 USA

Manufactured by:
Bausch Health Companies Inc.
Laval, Quebec H7L 4A8, Canada
U.S. Patent Numbers: 6,517,847; 8,809,307; 10,251,895 and 10,478,502

DUOBRII is a trademark of Bausch Health Companies Inc. or its affiliates.

© 2020 Bausch Health Companies Inc. or its affiliates

9645602

Patient Package Insert

TEAR HERE (Patient Information)

PATIENT INFORMATION
DUOBRII® (DEW-oh-bree)
(halobetasol propionate and tazarotene) lotion, for topical use

Important information: DUOBRII is for use on skin only. Do not apply DUOBRII in your mouth, eyes, or vagina.

What is the most important information I should know about DUOBRII?

DUOBRII may cause birth defects if used during pregnancy.
Females must not be pregnant when they start using DUOBRII or become pregnant during treatment with DUOBRII.

- For females who are able to get pregnant:
  - Your healthcare provider will order a pregnancy test for you within 2 weeks before you begin treatment with DUOBRII to be sure that you are not pregnant. Your healthcare provider will decide when to do the test.
  - Begin treatment with DUOBRII during a normal menstrual period.
  - Use an effective form of birth control during treatment with DUOBRII. Talk with your healthcare provider about birth control options that may be used to prevent pregnancy during treatment with DUOBRII.
  - Stop using DUOBRII and tell your healthcare provider right away if you become pregnant during treatment with DUOBRII.

What is DUOBRII?

DUOBRII is a prescription medicine used on the skin (topical) to treat adults with plaque psoriasis.
It is not known if DUOBRII is safe and effective in children under 18 years of age.

Do not use DUOBRII if you:

- are pregnant. See “What is the most important information I should know about DUOBRII?”

Before using DUOBRII, tell your healthcare provider about all of your medical conditions, including if you:

- have eczema or any other skin problems.
- have a skin infection. You may need medicine to treat the skin infection before using DUOBRII.
- have diabetes.
- have adrenal gland problems.
- have liver problems.
- are breastfeeding or plan to breastfeed. It is not known if DUOBRII passes into your breast milk. If you use DUOBRII and breastfeed, do not apply DUOBRII to your nipple or areola to avoid getting DUOBRII into your baby’s mouth.

Tell your healthcare provider about all the medicines you take, including prescription and over-the-counter medicines, vitamins, and herbal supplements.

Especially tell your healthcare provider if you take corticosteroids by mouth, or injection, or use other products on your skin that contain corticosteroids.

Certain medicines may make your skin more sensitive to sunlight. Ask your healthcare provider for a list of these medicines if you are not sure.

How should I use DUOBRII?

- Use DUOBRII exactly as your healthcare provider tells you to use it.
- If you shower or bathe before applying DUOBRII, your skin should be dry before applying the lotion.
- Apply a thin layer of DUOBRII to the affected areas 1 time each day and rub in gently.
- You should not use more than 50 grams of DUOBRII in 1 week.
- Avoid using DUOBRII on your face, groin, or underarms (armpits).
- Do not bandage, wrap, or cover the treated skin area(s) unless your healthcare provider tells you to.

What should I avoid during treatment with DUOBRII?

- Avoid sunlight, including sunlamps and tanning beds during your treatment with DUOBRII. DUOBRII can make your skin more sensitive to the sun and the light from sunlamps and tanning beds. You could get severe sunburn. Use sunscreen, and wear a hat and clothes that cover your skin if you have to be in sunlight.
- Talk to your healthcare provider if you get sunburn during treatment with DUOBRII. If you do get sunburn, do not use DUOBRII until your sunburn is healed.
- Avoid using DUOBRII on skin with eczema because it may cause severe irritation.

What are the possible side effects of DUOBRII?

DUOBRII may cause side effects, including:

- See “What is the most important information I should know about DUOBRII?”
- DUOBRII can pass through your skin. Too much DUOBRII passing through your skin can cause adrenal glands to stop working.
- Cushing’s syndrome, a condition that happens when your body is exposed to too much of the hormone cortisol.
- High blood sugar (hyperglycemia).
- Effects of growth and weight in children.
- Skin irritation. DUOBRII may cause increased skin irritation. Tell your healthcare provider if you develop any skin irritation during your treatment with DUOBRII. If you develop skin irritation, your healthcare provider may tell you to interrupt or stop using DUOBRII, or tell you to use DUOBRII less often.
- Sensitivity to light and risk of sunburn. See “What should I avoid during treatment with DUOBRII?”
- Vision problems. DUOBRII may increase your chance of developing cataract(s) and glaucoma. Tell your healthcare provider if you have blurred vision or other vision problems during your treatment with DUOBRII.

The most common side effects of DUOBRII include: redness, itching, swelling, burning, stinging, application site pain, inflamed hair follicles (folliculitis), thinning of the skin (atrophy), peeling and rash.

These are not all of the possible side effects of DUOBRII.

Call your doctor for medical advice about side effects. You may report side effects to FDA at 1-800-FDA-1088.

How should I store DUOBRII?

- Store DUOBRII at room temperature between 68°F to 77°F (20°C to 25°C).
- Protect from freezing.

Keep DUOBRII and all medicines out of the reach of children.

General information about the safe and effective use of DUOBRII

Medicines are sometimes prescribed for purposes other than those listed in a Patient Information leaflet. Do not use DUOBRII for a condition for which it was not prescribed. Do not give DUOBRII to other people, even if they have the same condition you have. It may harm them. You can ask your pharmacist or healthcare provider for information about DUOBRII that is written for health professionals.

What are the ingredients in DUOBRII?

Active ingredients: halobetasol propionate and tazarotene

Inactive ingredients: carbomer copolymer type B, carbomer homopolymer type A, diethyl sebacate, edetate disodium dihydrate, light mineral oil, methylparaben, propylparaben, purified water, sodium hydroxide, sorbitan monooleate and sorbitol solution, 70%.

Distributed by: Bausch Health US, LLC, Bridgewater, NJ 08807 USA
Manufactured by: Bausch Health Companies Inc., Laval, Quebec H7L 4A8, Canada

U.S. Patent Numbers: 6,517,847; 8,809,307; 10,251,895 and 10,478,502

DUOBRII is a trademark of Bausch Health Companies Inc. or its affiliates.

© 2020 Bausch Health Companies Inc. or its affiliates

For more information call 1-800-321-4576

This Patient Information has been approved by the U.S. Food and Drug Administration.

Revised: 01/2020

9645602

Package/Label Display Panel

NDC 0187-0653-01

Duobrii®
(halobetasol propionate
and tazarotene) Lotion
0.01%/ 0.045%

Rx only
Net Wt. 100g

For Topical Use Only
Not for Eye Use

Ortho Dermatologics